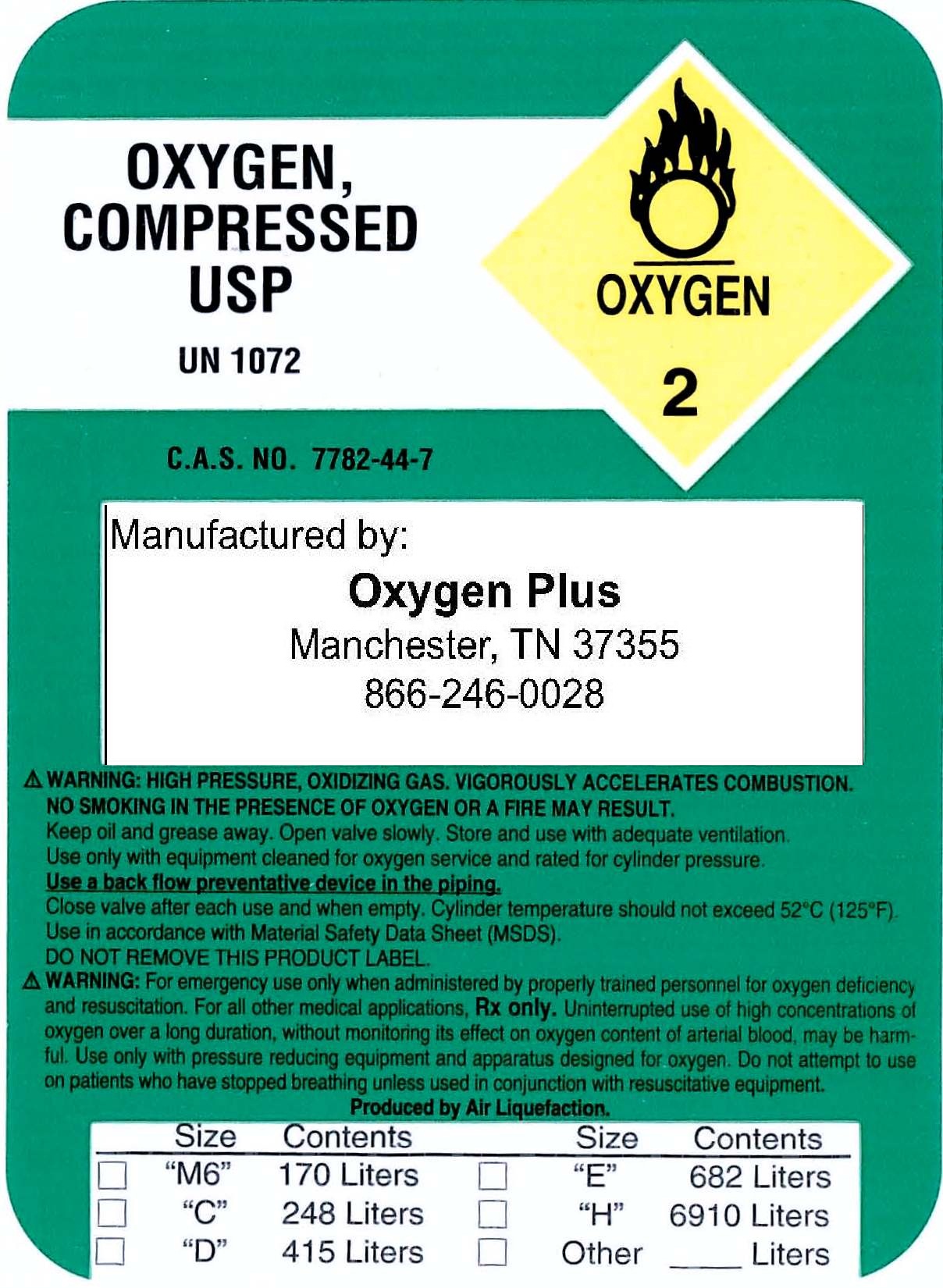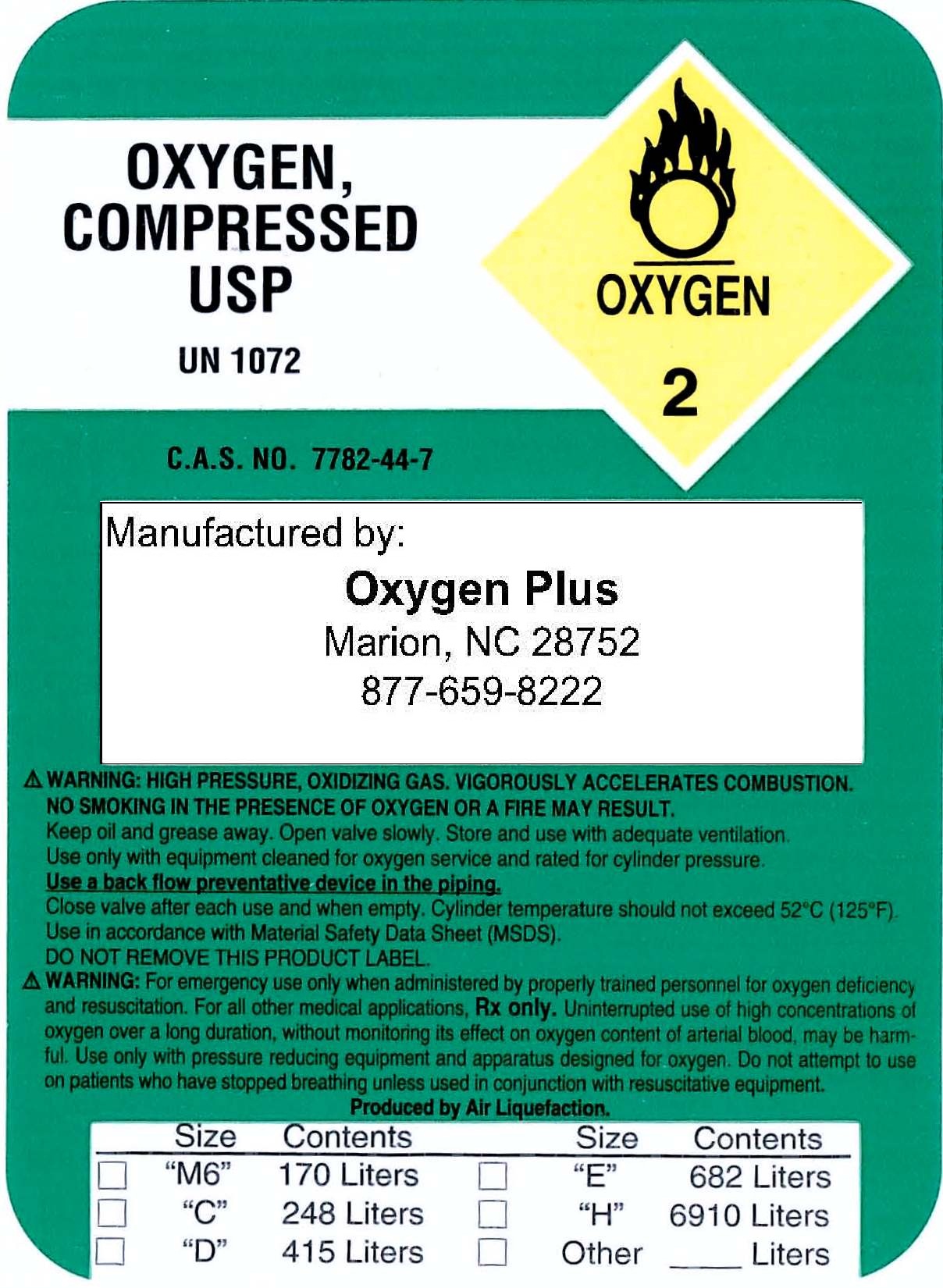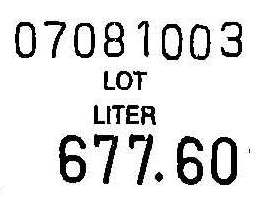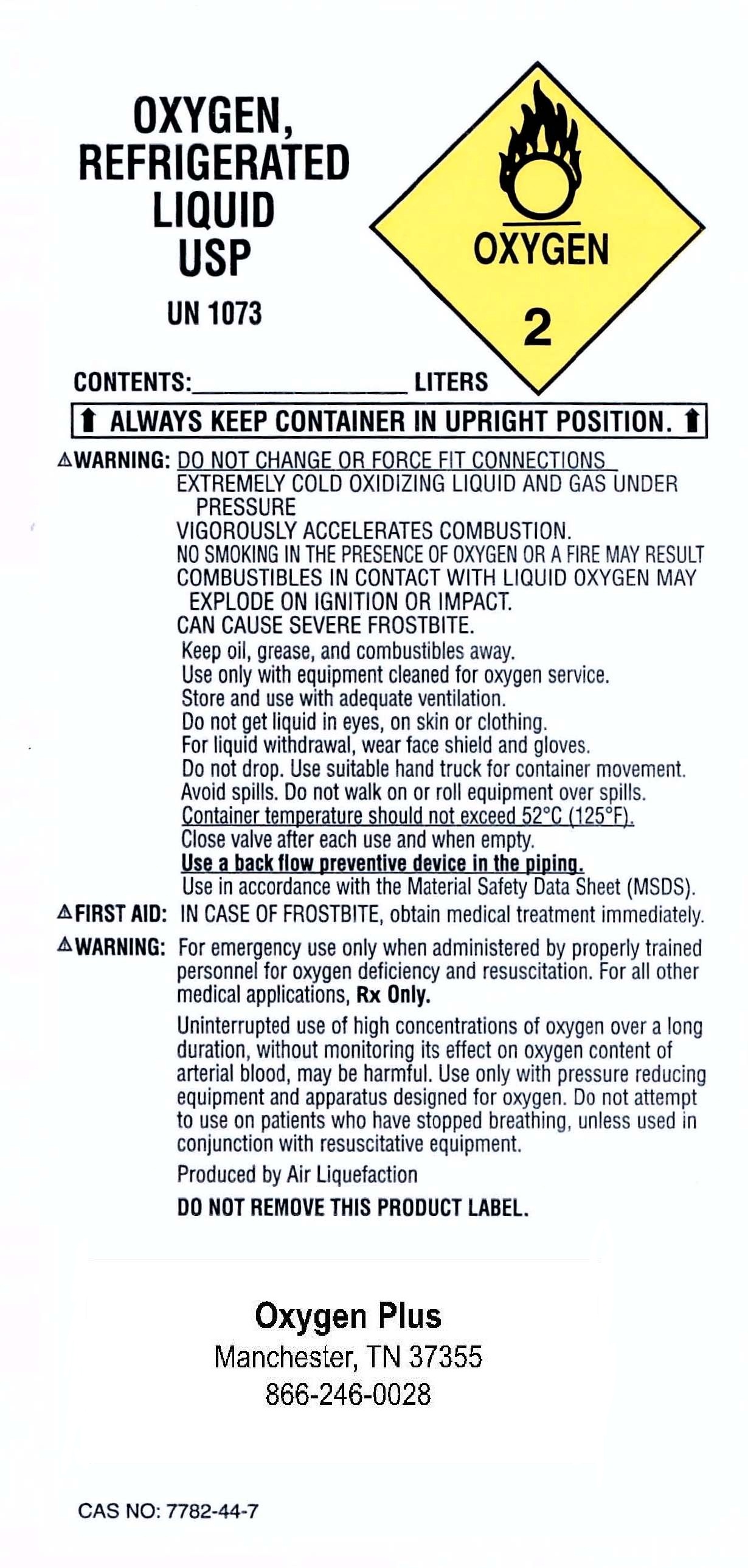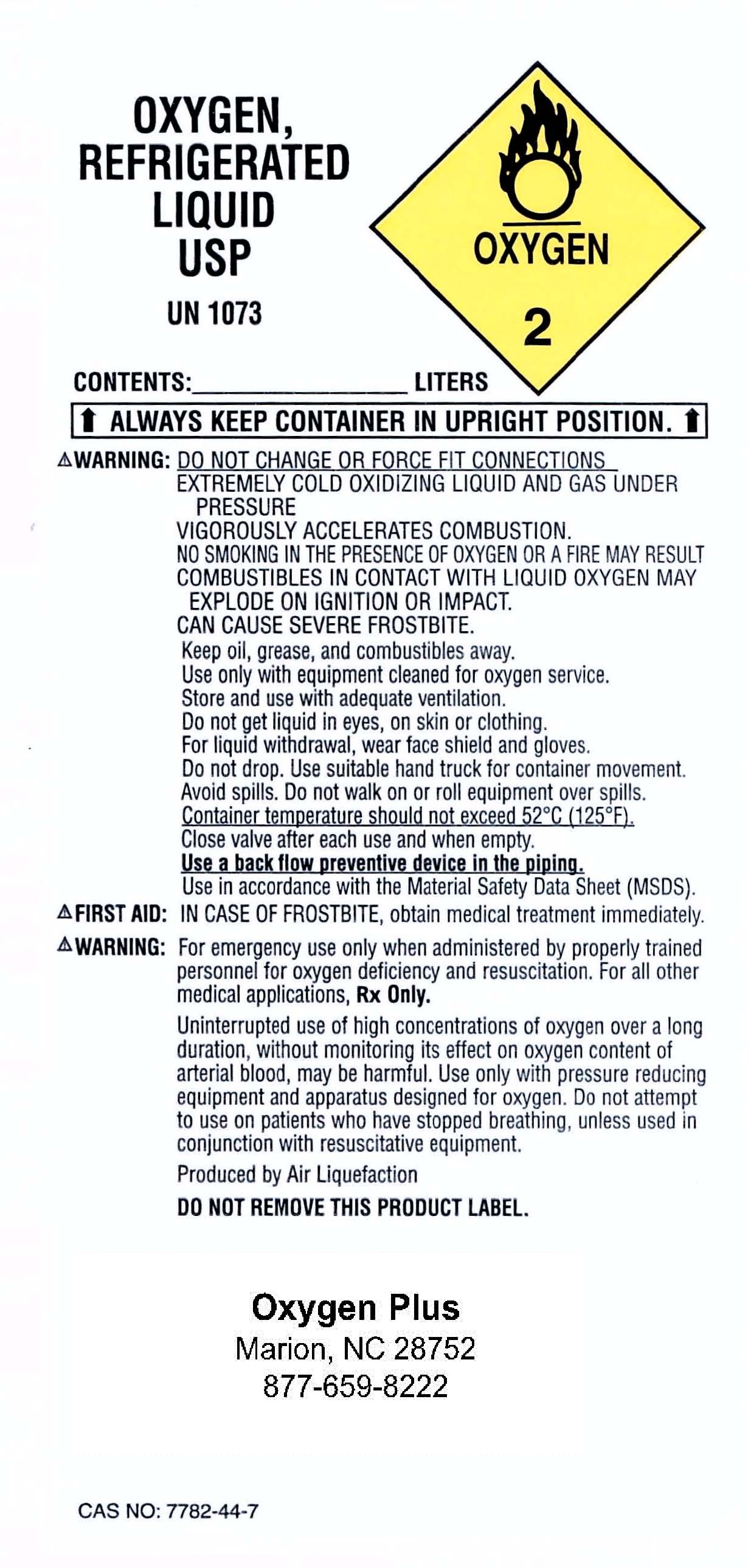 DRUG LABEL: Oxygen
NDC: 67777-001 | Form: GAS
Manufacturer: Oxygen Plus
Category: prescription | Type: HUMAN PRESCRIPTION DRUG LABEL
Date: 20100719

ACTIVE INGREDIENTS: Oxygen 99 L/100 L

Oxygen